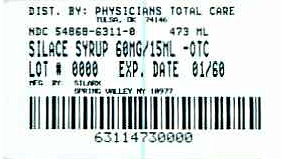 DRUG LABEL: Silace
NDC: 54868-6311 | Form: SYRUP
Manufacturer: Physicians Total Care, Inc.
Category: otc | Type: HUMAN OTC DRUG LABEL
Date: 20110614

ACTIVE INGREDIENTS: Docusate sodium 60 mg/15 mL
INACTIVE INGREDIENTS: alcohol ; citric acid; D&C red no. 33; FD&C red no. 40; glycerin; methylparaben; propylene glycol; propylparaben; water; sodium benzoate; sodium citrate; sucrose

Silace syrup

Active Ingredient: Docusate sodium 60 mg (in each 15 mL (1 tablespoonful))

Purpose: Stool Softener

Uses

- for gentle, reliable relief from occasional constipation (irregularity)

- generally produces bowel movement in 12 to 72 hours

Warnings

- Do not use

- laxative products for longer than 1 week unless told to do so by a doctor
- Do not use if you are presently taking mineral oil unless told to do by a doctor

Ask a doctor before use if you have

- stomach pain

- nausea

- vomiting

- noticed a sudden change in bowel habits that last over two weeks

Stop use and ask a doctor if you have rectal bleeding or fail to have a bowel movement after use of a laxative. These could be signs of a serious condition

If pregnant or breast feeding,

ask a health professional before use.

Keep out of reach of children. In case of overdose, get medical help or contact a Poison Control Center right away.

Directions

- take as directed by a doctor

- doses must be given in a 6-8 oz glass of milk or fruit juice, to prevent throat irritation

- dose may be taken as a single daily dose or in divided doses

- dosage should be adjusted to individual response

Adults and children 12 years of age and older | 1 to 6 tablespoonfuls, or as directed by a doctor
Children 6 to under 12 years of age | 1 to 2 1/2 tablespoonfuls, or as directed by a doctor
Children under 6 years | Ask a doctor

Other information

- store at room temperature 20°-25°C (68°-77°F)

- protect from freezing and excessive heat

- do not use if tamper-evident safety seal around cap is broken or missing

- dispense in tight, light-resistant container with a child-resistant closure

Inactive ingredients:

alcohol not more than 1%, citric acid, D&C red no. 33, FD&C red no. 40, peppermint flavor, glycerin, methylparaben, propylene glycol, propylparaben, purified water, sodium benzoate, sodium citrate, sucrose.

Questions

888-974-5279

Manufactured by:

Silarx Pharmaceutical, Inc.

19 West Street

Spring Valley , NY 10977-USA.

Relabeling of additional barcode by:
Physicians Total Care, Inc.
Tulsa, OK 74146

PACKAGE LABEL

SILACE (docusate sodium) syrup

473 mL (1 Pint)

NDC 54868-6311-0